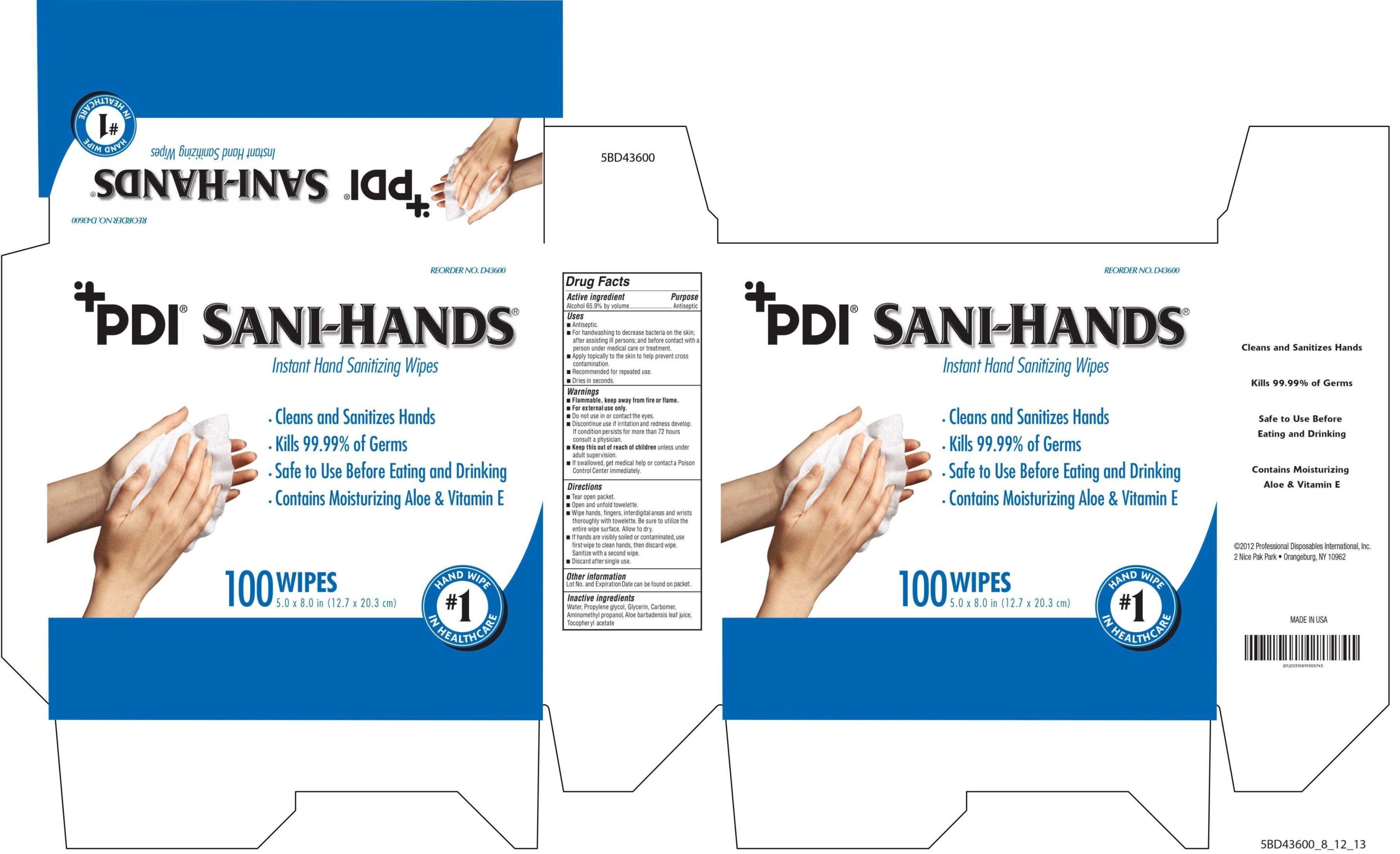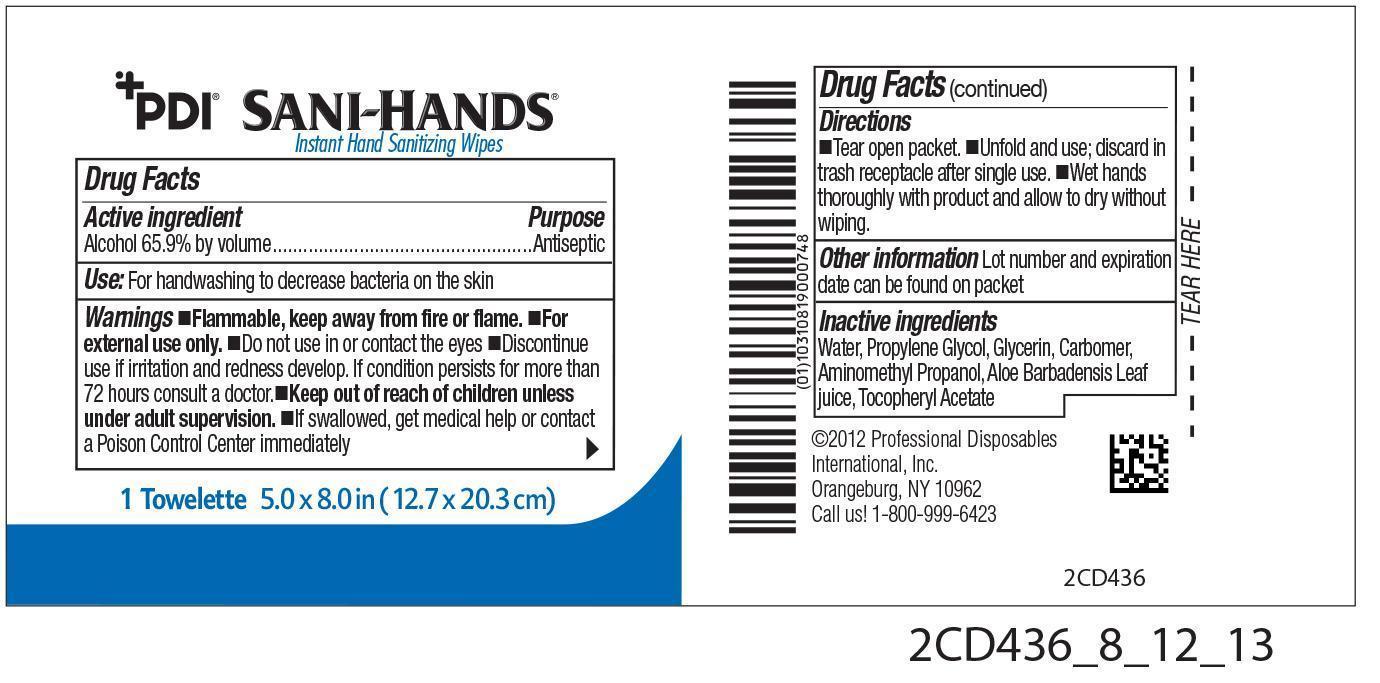 DRUG LABEL: PDI Sani-Hands
NDC: 10819-5813 | Form: CLOTH
Manufacturer: Professional Disposables International, Inc.
Category: otc | Type: HUMAN OTC DRUG LABEL
Date: 20131127

ACTIVE INGREDIENTS: Alcohol 0.659 mL/1 1
INACTIVE INGREDIENTS: WATER; PROPYLENE GLYCOL; GLYCERIN; CARBOMER HOMOPOLYMER TYPE C; AMINOMETHYL PROPANEDIOL; ALOE VERA LEAF; ALPHA-TOCOPHEROL ACETATE

Uses

- Antiseptic
- For hand washing to decrease bacteria on the skin; after assisting ill persons; and before contact with a person under medical care or treatment
- Apply topically to the skin to help prevent cross-contamination
- Recommended for repeated use.
- Dries in seconds

Warnings

- Flammable, keep away from fire or flame.
- For external use only.
- Do not use in or contact the eyes.
- Discontinue use if irritation and redness develop. If condition persist for more than 72 hours consult a physician.
- If swallowed, get medical help or contact a Poison Control Center immediately.

- Keep out of reach of children unless under adult supervision.

Directions

- Tear open packet.
- Open and unfold towelette.
- Wipe hands, fingers, interdigital areas and wrists thoroughly with towelettes. Be sure to utilize the entire wipe surface. Allow to dry.
- If hands are visibly soiled or contaminated, use first wipe to clean hands, then discard wipe. Sanitize with a second wipe.
- Discard after single use.

Other information

Lot No. and Expiration Date can be found on packet.

Dosage

If hands are visibly soiled or contaminated, use first wipe to clean hands, then discard wipe. Sanitize with a second wipe. Discard after single use.

Inactive ingredients

Water, Propylene Glycol, Glycerin, Carbomer, Aminometyl Propanol, Aloe Barbadensis Leaf Juice, Tocopheryl Acetate

Professional Disposables International, Inc.
Orangeburg, NY 10962
Call us! 1-800-999-6423

Made in USA

Principal Display Panel - 100 Packets per Box

PDI Sani-Hands(R)
Instant Hand Sanitizing Wipes

- Cleans and Sanitizes Hands
- Kills 99.99% of Germs
- Safe to Use Before Eating and Drinking
- Contains Moisturizing Aloe and Vitamine E

100 Wipes
5.0 x 8.0 in (12.7 x 20.3 cm)

#1 Hand Wipe in Healthcare

Packet Label
Box Label

Active ingredient

Alcohol 65.9% by volume

Purpose

Antiseptic